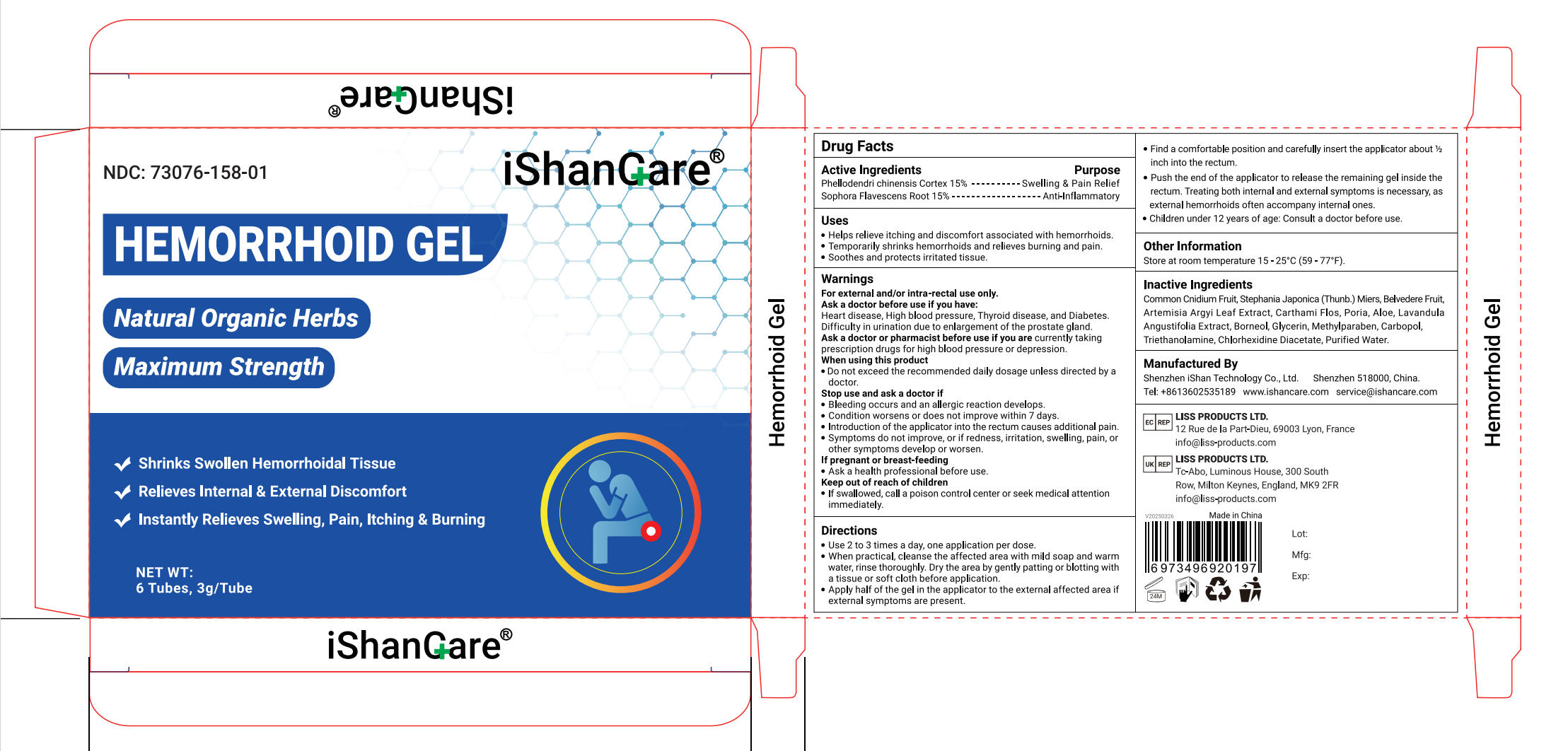 DRUG LABEL: iShanCare HEMORRHOID
NDC: 73076-183 | Form: GEL
Manufacturer: Shenzhen Ishan Technology Co., Ltd
Category: otc | Type: HUMAN OTC DRUG LABEL
Date: 20260212

ACTIVE INGREDIENTS: SOPHORA FLAVESCENS ROOT 15 g/100 g; PHELLODENDRINE 15 g/100 g
INACTIVE INGREDIENTS: CNIDIUM MONNIERI FRUIT; STEPHANIA JAPONICA WHOLE; ARTEMISIA ARGYI LEAF; WATER; CARTHAMUS TINCTORIUS FLOWER OIL; CARBOPLATIN; LAVANDULA ANGUSTIFOLIA WHOLE; WOLFIPORIA COCOS WHOLE; BORNEOL; CHLORHEXIDINE DIACETATE; GLYCERIN; METHYL PARAOXON; CUPRIC TRIETHANOLAMINE; ALOE; BASSIA SCOPARIA WHOLE

Active ingredients

Phellodendri chinensis Cortex 15%--------Swelling & Pain Relief

Sophora Flavescens Root15%---------Anti-Inflammatory

Inactive Ingredients

Common Cnidium Fruit, Stephania Japonica (Thunb.) Miers, Belvedere Fruit,Artemisia Argyi Leaf Extract, Carthami Flos, Poria, Aloe, LavandulaAngustifolia Extract, Borneol, Glycerin, Methylparaben, Carbopol,Triethanolamine,Chlorhexidine Diacetate, Purified Water.

Uses

·Helps relieve itching and discomfort associated with hemorrhoids.
·Temporarily shrinks hemorrhoids and relieves burning and pain.
. Soothes and protects irritated tissue.

Warnings

For external and / or intra-rectal use only.

When using this product

Do not exceed the recommended daily dosage unless directed by a
doctor.

Stop use

Bleeding occurs and an allergic reaction develops.

Condition worsens or does not improve within 7 days.

Introduction of the applicator into the rectum causes additional pain.

Symptoms do not improve, or if redness, irritation, swelling, pain, orother symptoms develop or worsen.

Ask a doctor

Heart disease, High blood pressure, Thyroid disease, and Diabetes Difficulty in urination due to enlargement of the prostate gland.

Keep out of reach of children

If swallowed, call a poison control center or seek medical attention immediately.

Dosage and administration

Use 2 to 3 times a day, one application per dose.

When practical, cleanse the affected area with mild soap and warmwater, rinse thoroughly.Dry the area by gently patting or blotting witha tissue or soft cloth before application.

Apply half of the gel in the applicator to the external affected area ifexterna symptoms are present.

Other information

Store at room temperature 15-25°C(59-77°F)

Directions:

Use 2 to 3 times a day, one application per dose.

When practical, cleanse the affected area with mild soap and warmwater, rinse thoroughly.Dry the area by gently patting or blotting witha tissue or soft cloth before application.

Apply half of the gel in the applicator to the external affected area ifexterna symptoms are present.